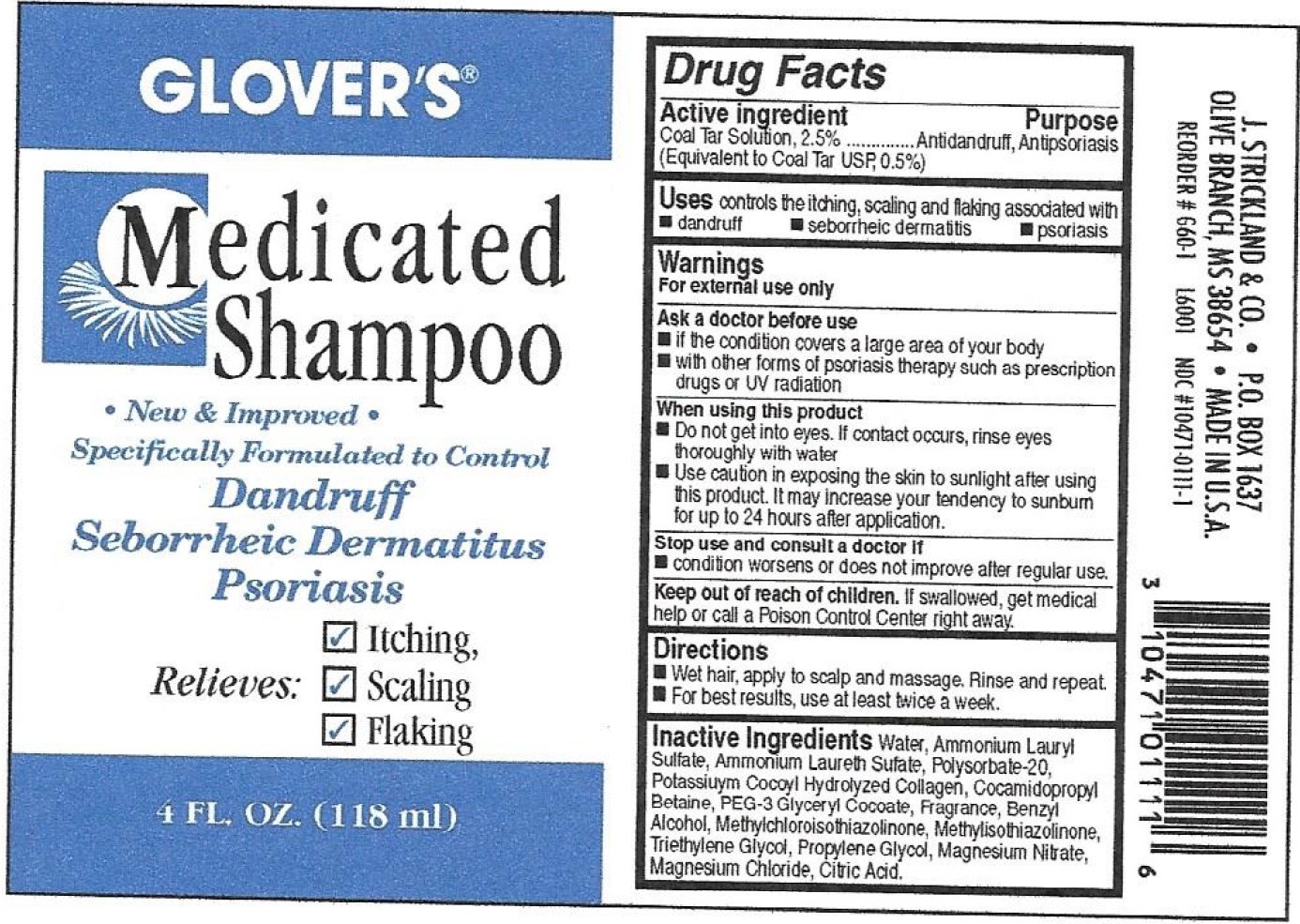 DRUG LABEL: Glovers Medicated Anti-Dandruff
NDC: 12022-010 | Form: SHAMPOO
Manufacturer: J. Strickland & Co.
Category: otc | Type: HUMAN OTC DRUG LABEL
Date: 20231021

ACTIVE INGREDIENTS: COAL TAR 25 mg/1 mL
INACTIVE INGREDIENTS: WATER; AMMONIUM LAURYL SULFATE; POLYSORBATE 20; COCAMIDOPROPYL BETAINE; BENZYL ALCOHOL; METHYLCHLOROISOTHIAZOLINONE; METHYLISOTHIAZOLINONE; TRIETHYLENE GLYCOL; PROPYLENE GLYCOL; MAGNESIUM NITRATE; MAGNESIUM CHLORIDE; CITRIC ACID MONOHYDRATE

Glover's Medicated Anti-Dandruff Shampoo

Active Ingredients

Coal Tar Solution, 2.5%

Purpose

Antidandruff, Antipsoriasis (Equivalent to Coal Tar USP, 0.5%)

Uses:

Controls scalp itching and flaking due to dandruff

Warnings:

For external use only

Ask A doctor before use

- if the condition covers a large area of your body
- with other forms of psoriasis therapy such as prescription drugs or UV radition

When using this product

- Do not get into eyse. If contact occurs, rinse eyes thoroughly with water
- Use caution in exposing the skin to sunlight after using this product. It may increase your tendency to sunburn for up to 24 hours after application.

Stop use and consult a doctor if

- condition worsens or does not improve after regular use.

Keep out of reach of children.

If swallowed, get medical help or call a Poison Control Center right away.

Directions

- Wet hair, apply to scalp and massage. Rinse and repeat.
- For best results, use at least twice a week.

Inactive Ingredients

Water, Ammonium Lauryl Sulfate, Ammonium Laureth Sufate, Polysorbate-20, Potassiuym Cocoyl Hydrolyzed Collagen, Cocamidopropyl Betaine, PEG-3 Glyceryl Cocoate, Fragrance, Benzyl Alcohol, Methylchloroisothiazolinone, Methylisothiazolinone, Triethylene Glycol, Propylene Glycol, Magnesium Nitrate, Magnesium Chloride, Citric Acid.